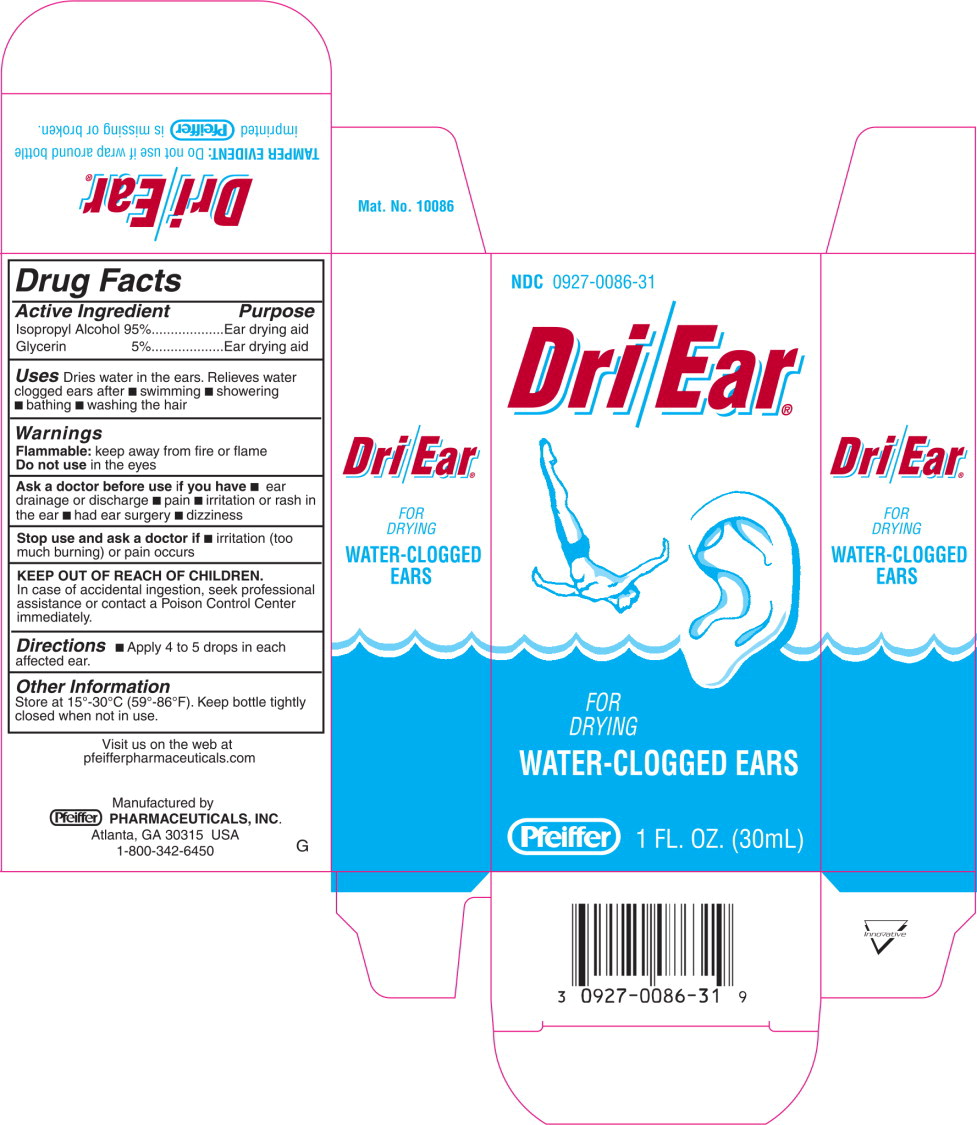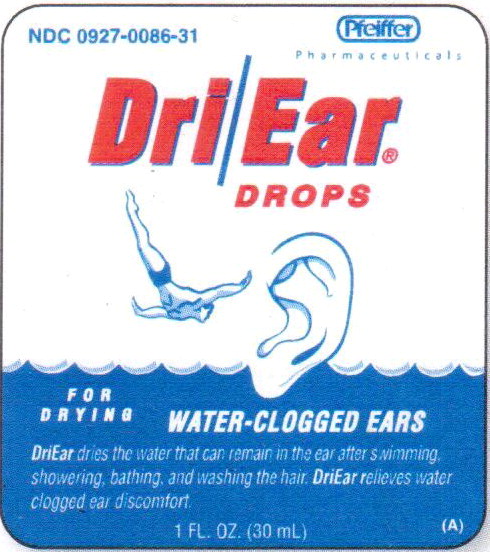 DRUG LABEL: Dri-Ear Drops
NDC: 0927-0086 | Form: LIQUID
Manufacturer: Pfeiffer Pharmaceuticals, Inc
Category: otc | Type: HUMAN OTC DRUG LABEL
Date: 20190731

ACTIVE INGREDIENTS: ISOPROPYL ALCOHOL 0.76 g/1 mL
INACTIVE INGREDIENTS: GLYCERIN

Drug Facts

Active Ingredient

Isopropyl Alcohol 95%

INACTIVE INGREDIENT

Glycerin 5%

Purpose

Ear drying aid

Ear drying aid

Uses

Dries water in the ears. Relieves water clogged ears after

- swimming
- showering
- bathing
- washing the hair

Warnings

Flammable: keep away from fire or flame

Do not use in the eyes

Ask a doctor before use if you have

- ear drainage or discharge
- pain
- irritation or rash in the ear
- had ear surgery
- dizziness

Stop use and ask a doctor if

- irritation (too much burning) or pain occurs

KEEP OUT OF REACH OF CHILDREN.

In case of accidental ingestion, seek professional assistance or contact a Poison Control Center immediately.

Directions

- Apply 4 to 5 drops in each affected ear.

Other Information

Store at 15°-30°C (59°-86° F). Keep bottle tightly closed when not in use.

Principal Display Panel - 30 mL Carton Label

NDC 0927-0086-31

Dri/Ear®

FOR
DRYING

WATER-CLOGGED EARS

Pfeiffer

1 FL. OZ. (30 mL)

Principal Display Panel - 30 mL Bottle Label

NDC 0927-0086-31

Pfeiffer

Pharmaceuticals

Dri/Ear®

DROPS

FOR
DRYING

WATER-CLOGGED EARS

DriEar dries the water that can remain in the ear after swimming, showering, bathing, and washing the hair. DriEar relieves water clogged ear discomfort.

1 FL. OZ. (30 mL)

(A)